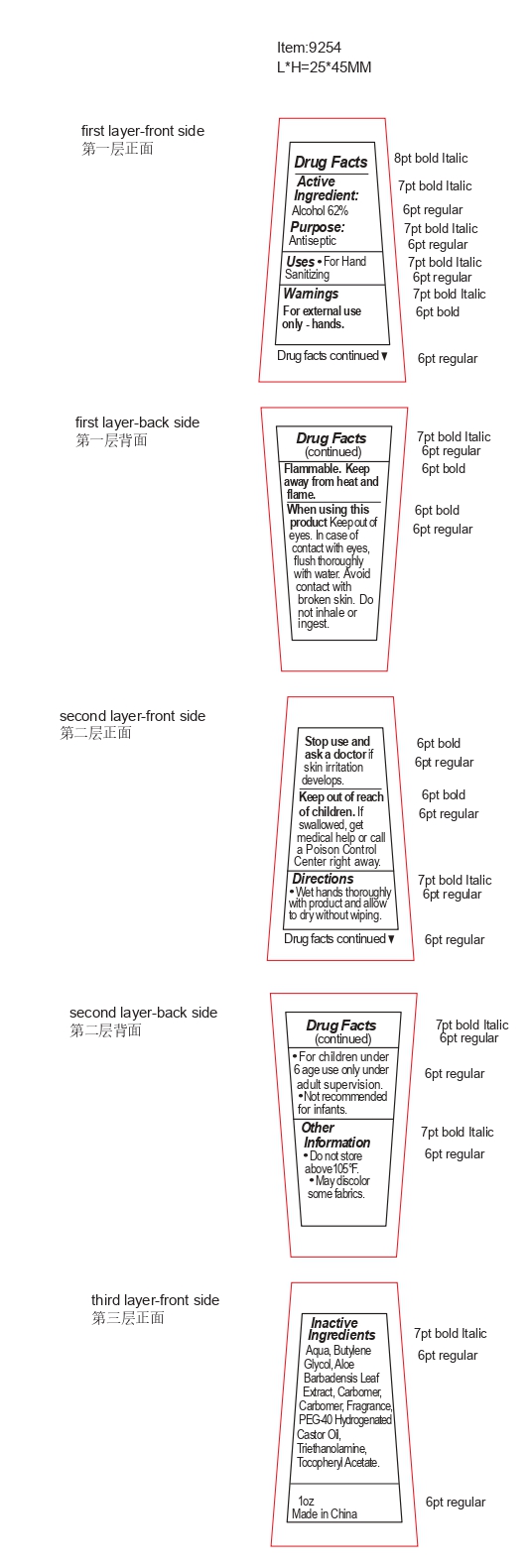 DRUG LABEL: antibacterial hand sanitizer gel
NDC: 82953-022 | Form: GEL
Manufacturer: Cosmuses Cosmetics (Ningbo) Co., Ltd.
Category: otc | Type: HUMAN OTC DRUG LABEL
Date: 20240821

ACTIVE INGREDIENTS: ALCOHOL 62 mL/100 mL
INACTIVE INGREDIENTS: FRAGRANCE 13576; .ALPHA.-TOCOPHEROL ACETATE; BUTYLENE GLYCOL; ALOE VERA LEAF; WATER; CARBOMER 940; TROLAMINE; POLYOXYL 40 HYDROGENATED CASTOR OIL

antibacterial hand sanitizer gel

Active Ingredients

Alcohol 62%

Purpose

Antiseptic

Uses

- For hand Sanitizing

Warnings

For external use only- hands.

Flammable. Keep away from heat and flame.

When using this product, keep out of eyes. In case of contact with eyes, flush thoroughly with water. Avoid contact with broken skin. Do not inhale or ingest.

Stop use and ask doctor if skin irritation develops.

Keep out of reach of children. If swallowed, get medical help or call a Poison Control Center right away.

Directions

- Wet hands throughly with product and allow to dry without wiping.
- For children under 6 age use only under adult supervision.
- Not recommended for infants.

Other information

- Do not store above 105oF.
- May discolor some fabrics.

Inactive Ingredients

Aqua, Butylene Glycol, Aloe Barbadensis Leaf Extract, Carbomer, Fragrance, PEG-40 Hydrogenated Castor Oil, Triethanolamine, Tocopheryl Acetate.